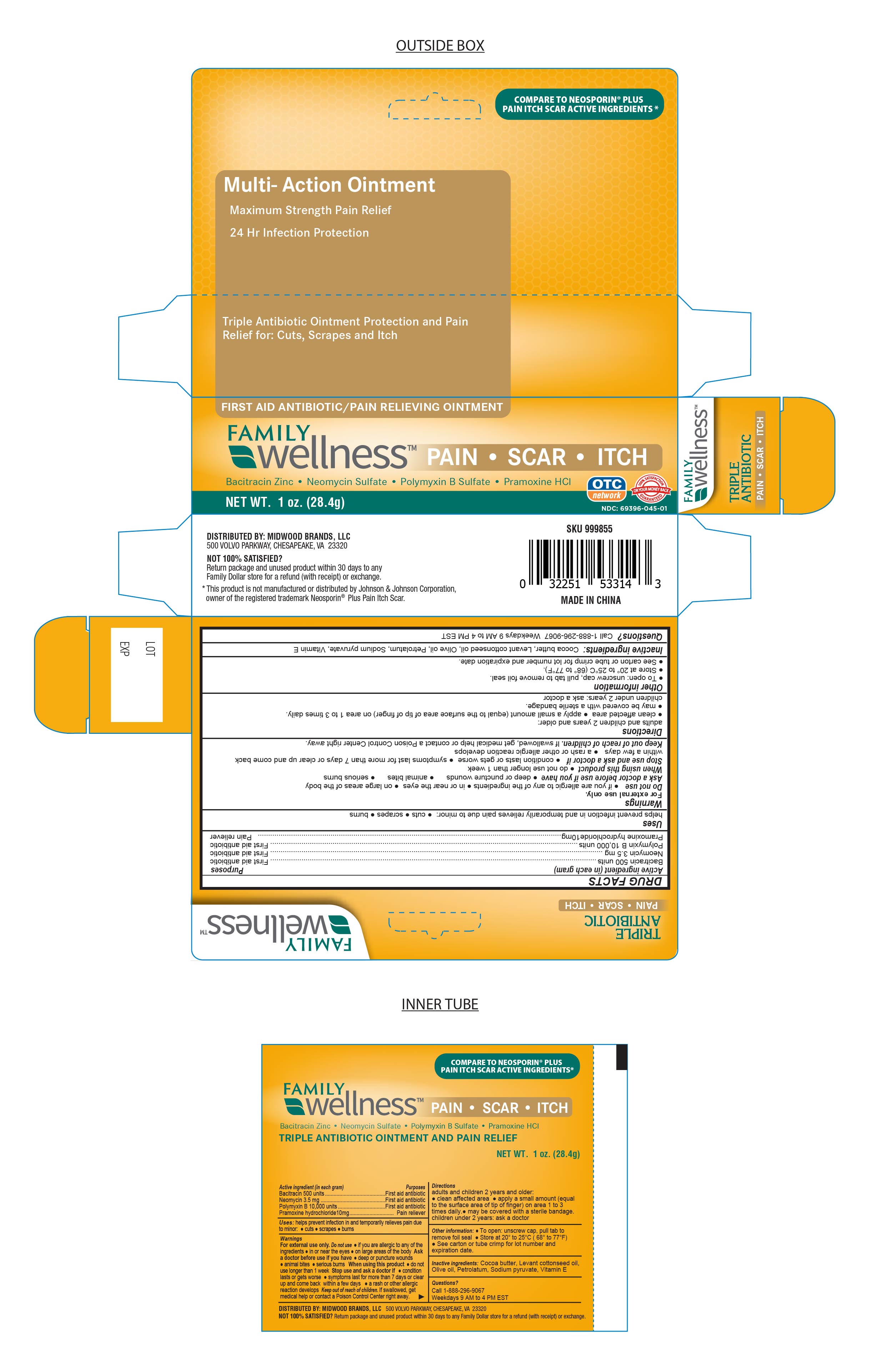 DRUG LABEL: Tripleantibioticapainscaritch
NDC: 69396-045 | Form: OINTMENT
Manufacturer: Trifecta Pharmaceutical USA LLC
Category: otc | Type: HUMAN OTC DRUG LABEL
Date: 20241220

ACTIVE INGREDIENTS: POLYMYXIN B SULFATE 10000 [USP'U]/100 g; BACITRACIN 500 [USP'U]/100 g; NEOMYCIN SULFATE 3.5 mg/100 g; PRAMOXINE HYDROCHLORIDE 10 mg/100 g
INACTIVE INGREDIENTS: SODIUM PYRUVATE; ALPHA-TOCOPHEROL; OLIVE OIL; PETROLATUM; LEVANT COTTONSEED OIL; COCOA BUTTER

Triple Antibiotic Pain Scar Itch

Active Ingredient

Bacitracin 500 Units

Purpose

First Aid Antibiotic

Active Ingredient

Neomycin 3.5mg

Purpose

First Aid Antibiotic

Active Ingredient

Polymyxin B 10,000 Units

Purpose

First Aid Antibiotic

Active Ingredient

Pramoxine HCL 10mg

Purpose

Pain Reliever

Uses

Helps prevent infection in and temporarily relieves pain due to minor cuts, scrapes and burns.

Warnings

For external use only. Do not use:

- If you are allergic to any of the ingredients
- in or near the eyes
- on large areas of the body

Ask a Doctor before Use

Ask Doctor before use if you have:

- Deep or puncture wouns
- Animal bites
- Serious burns

Stop Use and ask a Doctor if:

- Condition persists or gets worse
- Symptoms last for more than 7 days or clear up and come back within a few days
- A rash or other allergic reaction develops

When using this product

Do not use longer than 1 week

Keep out of Reach of Children

If Swallowed, get medical help or contact a Poison Control Center right away

Directions

Adults and children 2 years and older:

- Clean the affected area
- Apply a small amount of this product (an amount equal to the surface area of the tip of a finger) on the area 1 to 3 times daily
- May be covered with a sterile bandage

Children under 2 years: ask a doctor

Other Information

- To Open: Unscrew cap, pull tab to remove foil seal
- Store at 20° to 25°C (68° to 77°F)
- See carton or tube crimp for lot number and expiration date

Inactive Ingredient:

Cocoa Butter, Levant Cottonseed Oil, Olive Oil, Petrolatum, Sodium pyruvate, vitamin E

Questions?

Call 1-888-296-9067 Weekdays 9AM - 4PM EST

DISTRIBUTED BY: MIDWOOD BRANDS, LLC.

500 Volvo Parkway, Chesapeake, VA. 23320

NOT SATISFIED?

Return package and unused product within 30 days to any Family Dollar store for a refund (with receipt) or exchange.

This product is not manufactured or distributed by Johnson & Johnson Corporation, owner of the registered trademark Neosporin® Plus Pain Relief.